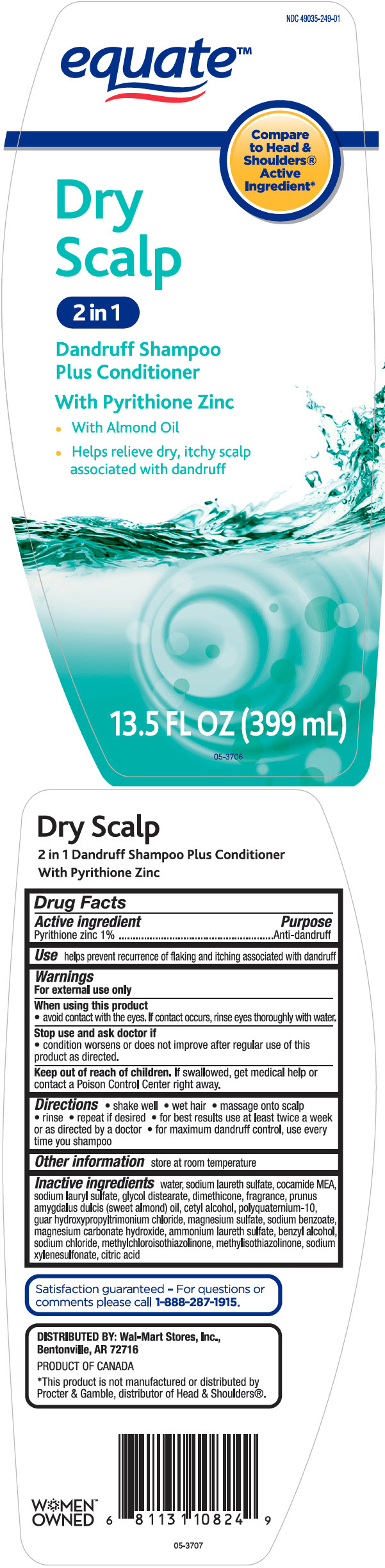 DRUG LABEL: Equate Dry Scalp 2 in 1 Dandruff
NDC: 49035-249 | Form: SHAMPOO
Manufacturer: Wal-Mart Stores, Inc.
Category: otc | Type: HUMAN OTC DRUG LABEL
Date: 20240201

ACTIVE INGREDIENTS: Pyrithione Zinc 10 mg/1 mL
INACTIVE INGREDIENTS: Water; SODIUM LAURETH-3 SULFATE; COCO MONOETHANOLAMIDE; Sodium Lauryl Sulfate; Glycol Distearate; Dimethicone; ALMOND OIL; Cetyl Alcohol; POLYQUATERNIUM-10 (30000 MPA.S AT 2%); GUAR HYDROXYPROPYLTRIMONIUM CHLORIDE (1.7 SUBSTITUENTS PER SACCHARIDE); MAGNESIUM SULFATE, UNSPECIFIED FORM; Sodium Benzoate; Magnesium Carbonate Hydroxide; AMMONIUM LAURETH-5 SULFATE; Benzyl Alcohol; Sodium Chloride; Methylchloroisothiazolinone; Methylisothiazolinone; Sodium Xylenesulfonate; CITRIC ACID MONOHYDRATE

Equate™ Dry Scalp 2 in 1 Dandruff SH & COND
Anti-Dandruff

Drug Facts

Active ingredient

Pyrithione Zinc 1%

Purpose

Anti-dandruff

Use

helps prevent recurrence of flaking and itching associated with dandruff.

Warnings

For external use only

When using this product

- avoid contact with the eyes. If contact occurs, rinse eyes thoroughly with water.

Stop use and ask a doctor if

- condition worsens or does not improve after regular use of this product as directed

Keep out of reach of children. If swallowed, get medical help or contact a Poison Control Center right away

Directions

- shake well
- wet hair
- massage onto scalp
- rinse
- repeat if desired
- for best results use at least twice a week or as directed by a doctor
- for maximum dandruff control, use every time you shampoo

Other information

store at room temperature

Inactive ingredients

water, sodium laureth sulfate, cocamide MEA, sodium lauryl sulfate, glycol distearate, dimethicone, fragrance, prunus amygdalus dulcis (sweet almond) oil, cetyl alcohol, polyquaternium-10, guar hydroxypropyltrimonium chloride, magnesium sulfate, sodium benzoate, magnesium carbonate hydroxide, ammonium laureth sulfate, benzyl alcohol, sodium chloride, methylchloroisothiazolinone, methylisothiazolinone, sodium xylenesulfonate, citric acid

QUESTIONS

Satisfaction guaranteed – For questions or comments please call 1-888-287-1915.

DISTRIBUTED BY: Wal-Mart Stores, Inc.,
Bentonville, AR 72716

PRINCIPAL DISPLAY PANEL - 399 mL Bottle Label

NDC 49035-249-01

equate™

Compare
to Head &
Shoulders®
Active
Ingredient*

Dry
Scalp

2 in 1

Dandruff Shampoo
Plus Conditioner

With Pyrithione Zinc

- With Almond Oil
- Helps relieve dry, itchy scalp
  associated with dandruff

13.5 FL OZ (399 mL)

05-3706